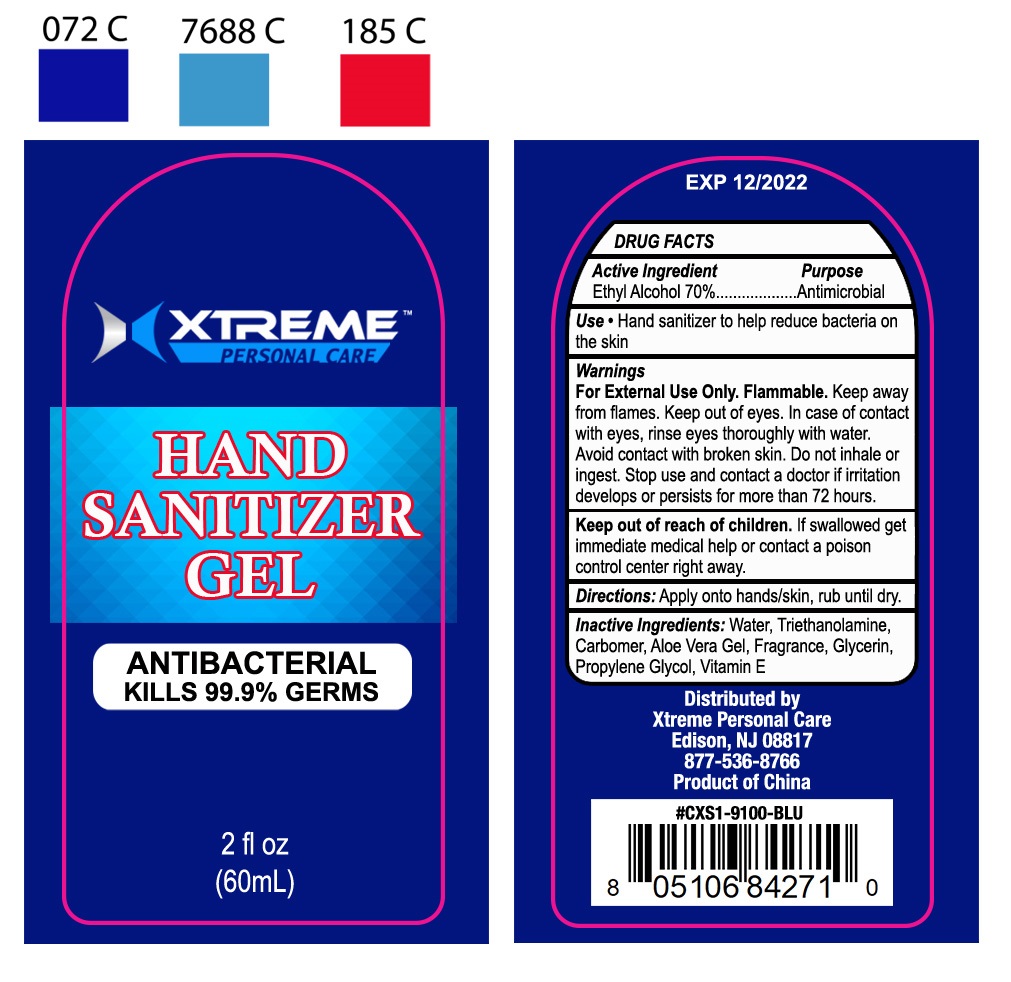 DRUG LABEL: XTREME PERSONAL CARE Hand Sanitizer
NDC: 75410-002 | Form: GEL
Manufacturer: Yiwu Story of Love Cosmetic Co., Ltd
Category: otc | Type: HUMAN OTC DRUG LABEL
Date: 20200528

ACTIVE INGREDIENTS: ALCOHOL 70 mL/100 mL
INACTIVE INGREDIENTS: GLYCERIN; CARBOMER 934; TROLAMINE; .ALPHA.-TOCOPHEROL ACETATE; ALOE VERA WHOLE; PROPYLENE GLYCOL

Active Ingredient(s)

Ethyl Alcohol 70% v/v

Purpose

Antimicrobial

Use

Hand sanitizer to help decrease bacteria on the skin that could cause disease

Warnings

For external use only. Flammable. Keep away from flame

When using this product keep out of eyes. In case of contact with eyes, rinse eyes thoroughly with water.

Do not inhale or ingest

Avoid contact with broken skin

Keep out of reach of children. If swallowed, get immediate medical help or contact a Poison Control Center right away

Directions

Apply onto hans skin, rub until dry

Inactive ingredients

Water, Triethanolamine, Carbomer, Aloe Vera Gel, Glycerin, Fragrance, Propylene Glycol, Vitamin E